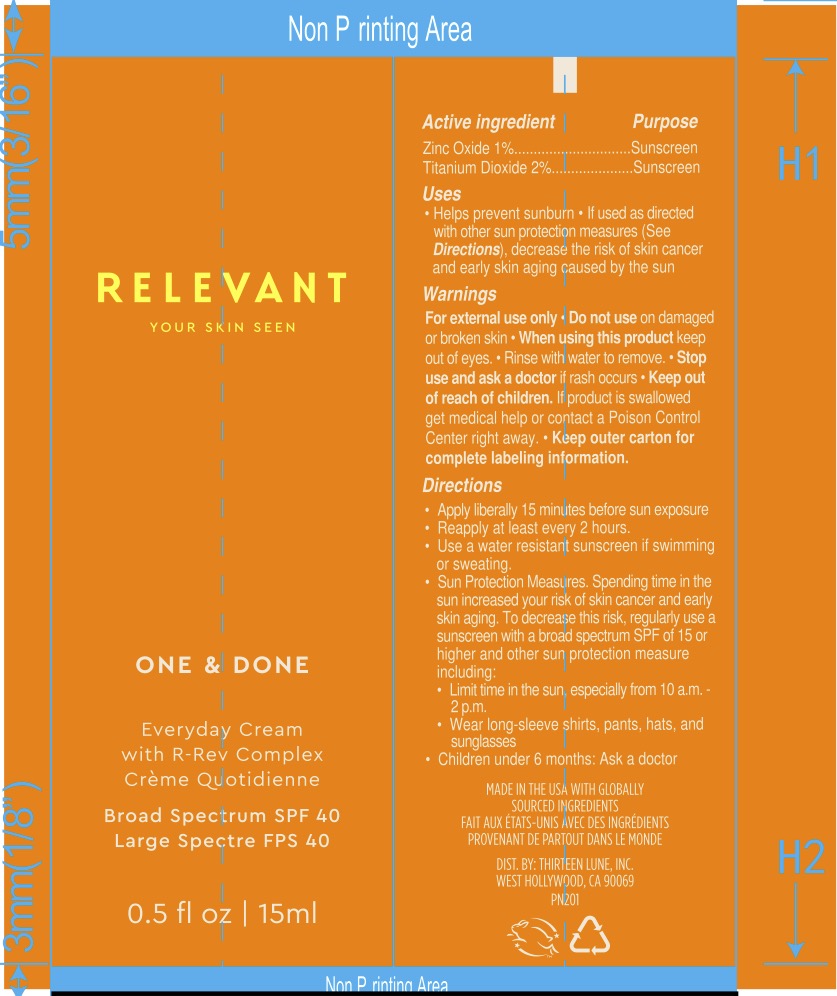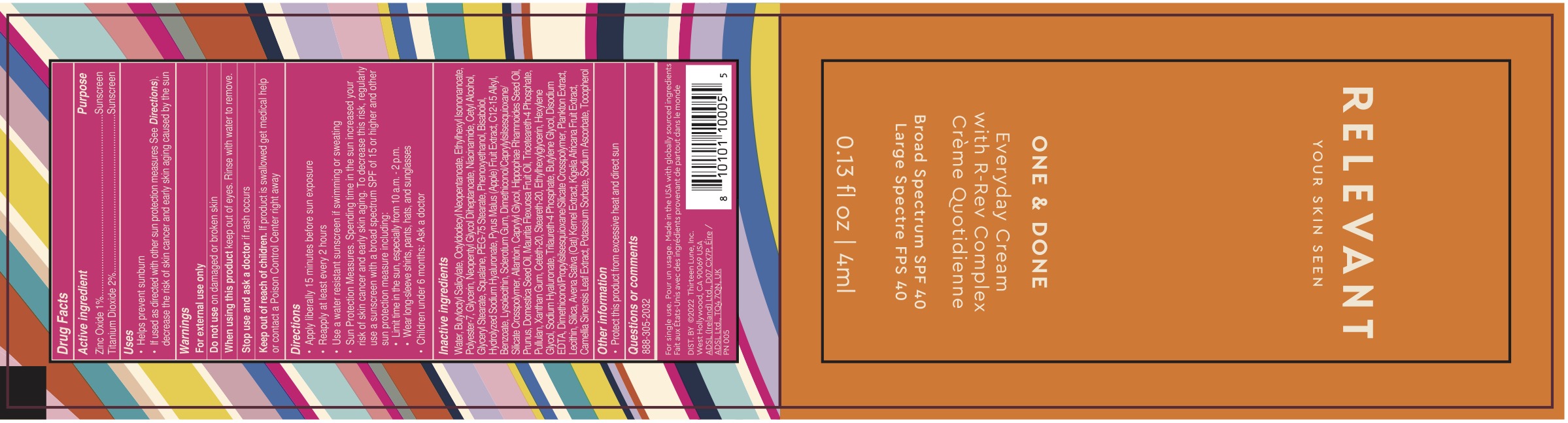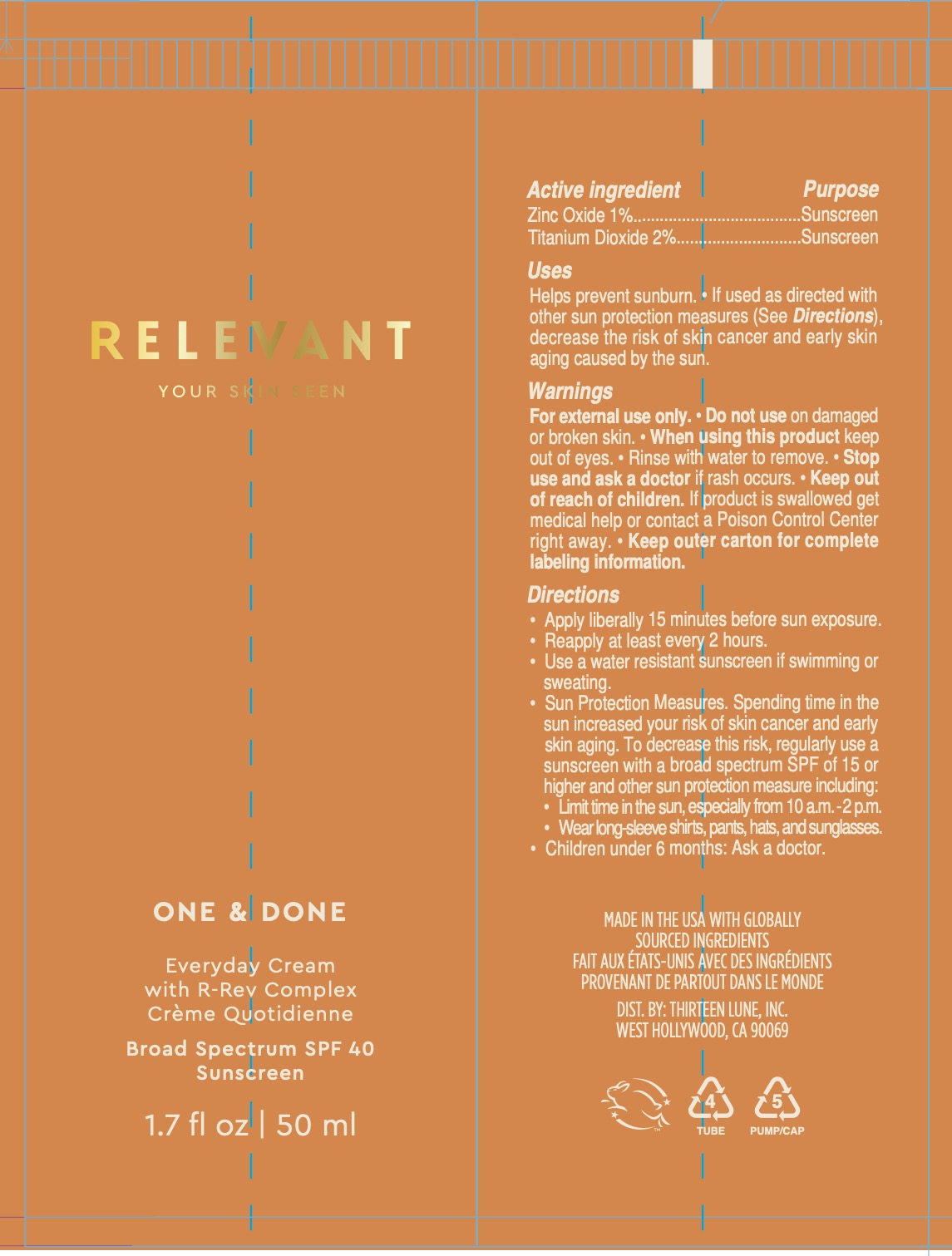 DRUG LABEL: One and Done
NDC: 82735-200 | Form: CREAM
Manufacturer: Thirteen Lune Inc.
Category: otc | Type: HUMAN OTC DRUG LABEL
Date: 20220525

ACTIVE INGREDIENTS: ZINC OXIDE 1 g/100 mL; TITANIUM DIOXIDE 2 g/100 mL
INACTIVE INGREDIENTS: WATER

Active Ingredient

ZINC OXIDE 1%

TITANIUM DIOXIDE 2%

Purpose

SUNSCREEN

Warnings

For external use only.

Do not use on damaged or broken skin.

When using this product keep out of eyes.

Rinse with water to remove.

Stop use and ask a doctor if rash occurs.

Keep out of reach of children.

If product is swallowed get medical help or contact a Poison Control Center right away.

Keep outer carton for complete labeling information.

Uses

Helps prevent sunburn.

If used as directed with other sun protection measures (See Directions), decrease the risk of skin cancer and early skin againg caused by the sun.

Directions

Apply liberally 15 minutes before sun exposure.

Reapply at least every 2 hours.

Use a water resistant sunscreen if swimming or sweating.

Sun Protection Measures. Spending time in the sun increased your risk of skin cancer and early skin aging. To decrease this rick, regularly use a sunscreen with a broad spectrum SPF of 15 or higher and other sun protection measure including:

- Limit time in the sun, especially from 10 a.m. - 2p.m.
- Wear long sleeve shirts, pants, hats and sunglasses.

Children under 6 months: Ask a doctor

Questions

(888) 305-2032

Inactive Ingredients

Water, Butyloctyl Salicylate, Octyldodecyl Neopentanoate, Ethylhexyl Isononanoate, Polyester-7, Glycerin, Neopentyl Glycol Diheptanoate, Niacinamide, Cetyl Alcohol, Glyceryl Stearate, Squalane, PEG-75 Stearate, Phenoxyethanol, Bisabolol, Hydrolyzed Sodium Hyaluronate, Pyrus Malus (Apple) Fruit Extract, C12-15 Alkyl, Benzoate, Lysolecithin, Sclerotium Gum, Dimethiconol/Caprylylsilsesquioxane/Silicate Crosspolymer, Allantoin, Caprylyl Glycol, Hippophae Rhamnoides Seed Oil, Prunus, Domestica Seed Oil, Mauritia Flexuosa Fruit Oil, Triceteareth-4 Phosphate, Pullulan, Xanthan Gum, Ceteth-20, Steareth-20, Ethylhexylglycerin, Hexylene Glycol, Sodium Hyaluronate, Trilaureth-4 Phosphate, Butylene Glycol, Disodium EDTA, Dimethiconol/Propylsilsesquioxane/Silicate Crosspolymer, Plankton Extract, Lecithin, Silica, Avena Sativa (Oat) Kernel Extract, Kigelia Africana Fruit Extract, Camellia Sinensis Leaf Extract, Potassium Sorbate, Sodium Ascorbate, Tocopherol.

KEEP OUT OF REACH OF CHILDREN.

Principal Display Panel

50ML RELEVANT ONE + DONE 50ML

15ML RELEVANT ONE + DONE SPF

4ML RELEVANT ONE + DONE SACHET (SAMPLE)